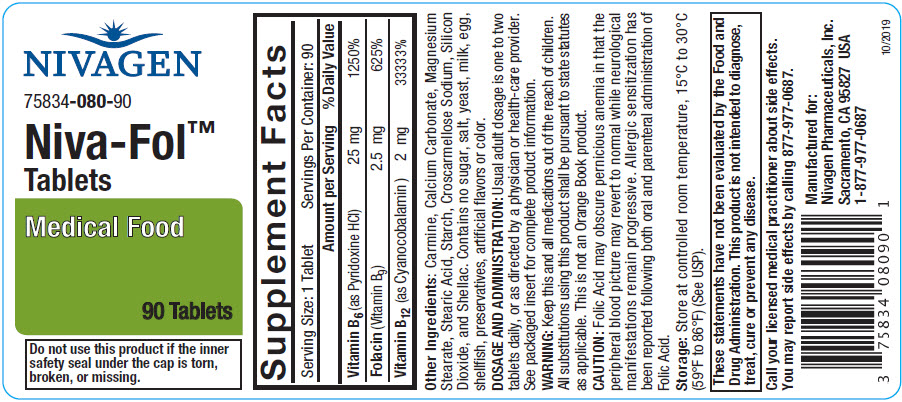 DRUG LABEL: Niva-Fol
NDC: 75834-080 | Form: TABLET
Manufacturer: Nivagen Pharmaceuticals, Inc.
Category: other | Type: DIETARY SUPPLEMENT
Date: 20210916

ACTIVE INGREDIENTS: Pyridoxine Hydrochloride 25 mg/1 1; Folic Acid 2.5 mg/1 1; Cyanocobalamin 2 mg/1 1
INACTIVE INGREDIENTS: Calcium Carbonate; Magnesium Stearate; Stearic Acid; Croscarmellose Sodium; Silicon Dioxide; Shellac

Niva-Fol™ Tablets

HEALTH CLAIM

Medical Food

STATEMENT OF IDENTITY

Each Niva-Fol™ Tablet contains:

Vitamin B6 (as Pyridoxine HCl) | 25 mg
Folacin (Folic Acid) | 2.5 mg
Vitamin B12 (as Cyanocobalamin) | 2 mg

Other Ingredients:

Carmine, Calcium Carbonate, Magnesium Stearate, Stearic Acid, Starch, Croscarmellose Sodium, Silicon Dioxide, and Shellac. Contains no sugar, salt, yeast, milk, egg, shellfish, preservatives, artificial flavors or color.

INDICATIONS AND USAGE

For the dietary management of individuals with distinct nutritional needs under a physician or health-care provider's supervision for hyperhomocysteinemia; with particular emphasis for individuals with or at risk for atherosclerotic vascular disease in the coronary^1, peripheral^2, or cerebral^3 vessels, or vitamin B12 deficiency^4. Niva-Fol™ Tablets are labeled as a medical food intended for use under active and ongoing medical supervision requiring medical care on a recurring basis for, among other things, instructions on the use of the medical food.

MEDICAL FOODS

Medical foods are Intended for the dietary management of a patient who, because of therapeutic or chronic medical needs, has limited or impaired capacity to ingest, digest, absorb, or metabolize ordinary foodstuffs or certain nutrients, or who has other special medically determined nutrient requirements, the dietary management of which cannot be achieved by the modification of a normal diet alone. Although a medical-food product is intended for use under the active and ongoing medical supervision, FDA does not require a prescription.

These statements have not been evaluated by the Food and Drug Administration. This product is not intended to diagnose, treat, cure or prevent any disease.

PRECAUTIONS

Folacin (folic acid) when administered as a single agent in doses above 0.1 mg daily, may obscure pernicious anemia in that hematologic remission can occur while neurological manifestations remain progressive. The 2 mg of cyanocobalamin contained in Niva-Fol™ Tablets has been shown to provide an adequate amount of cyanocobalamin to address this precaution^5. Unmetabolized folic acid has been shown in one study of 105 postmenopausal women (50-75 yrs) to have the potential to reduce natural killer cells' cytotoxicity, which may result in an impaired immune response^6.

Cyanocobalamin should not be used in those with Leber's optic atrophy. Decreased levels of B12 have been associated with reduced ability to detoxify the cyanide in exposed individuals and cyanocobalamin may increase the risk of irreversible neurological damage from optic atrophy in those affected with the disorder. Hydroxocobalamin can aid in the detoxification of cyanide. This form of B12 is an acceptable form for B12 supplementation in those with this disorder.

Pregnant women and nursing mothers should only use 12 microgram doses of B12 (cyanocobalamin) from nutritional supplements. Doses higher than this should only be recommended by your physician. Administration of doses of vitamin B12 greater than 10 micrograms daily may produce a hematological response in those with anemia secondary to folate deficiency.

If pregnant, or planning to become pregnant or are currently breast-feeding please contact your physician, or health-care provider before using or continuing use.

ADVERSE REACTIONS

Allergic sensitization has been reported following both oral and parenteral administration of folacin (folic acid). Paresthesia, somnolence, nausea and headaches have been reported with pyridoxine. Mild transient diarrhea, polycythemia vera, itching, transitory exanthema, and the feeling of swelling of the entire body has been associated with cyanocobalamin.

CONTRAINDICATIONS

Known hypersensitivity to any of the components in the product is a contraindication.

DRUG INTERACTIONS

Pyridoxine supplements should not be given to patients receiving the drug levodopa, because the action of levodopa is antagonized by pyridoxine. However, pyridoxine may be used concurrently in patients receiving a preparation containing both carbidopa and levodopa. Concurrent use of phenytoin and folacin (folic acid) may result in decreased phenytoin effectiveness.

PATIENT INFORMATION

Niva-Fol™ Tablets are for use only under the direction and supervision of a licensed physician or health-care provider.

DOSAGE AND ADMINISTRATION

Usual adult dosage is one to two tablets daily, or as directed by a physician or health-care provider.

HOW SUPPLIED

Niva-Fol™ Tablets are available as an oval, coated tablet, debossed "N080". Supplied in bottles of 90 Tablets, 75834-080-90

Store at 25°C (77°F); excursions permitted to 15°-30°C (59°-86°F).

See USP Controlled Room Temperature.

Protect from light and moisture.

Dispense in a tight, light-resistant container with a child-resistant closure as defined in the USP/NF.

SAFE HANDLING WARNING

WARNING: KEEP THIS AND ALL MEDICATIONS OUT OF THE REACH OF CHILDREN. IN CASE OF ACCIDENTAL OVERDOSE, SEEK PROFESSIONAL ASSISTANCE OR CONTACT A POISON CONTROL CENTER IMMEDIATELY.

Medical Food

All substitutions using this product shall be pursuant to state statutes as applicable. This is not an Orange Book product.

To report a serious adverse event contact: 1-877-977-0687

Manufactured for:
Nivagen Pharmaceuticals, Inc.
Sacramento, CA 95827

References

^(1, 2) Eikelboom JW, Lonn Eva, Genest Jr Jaques, Hankey Graeme, Yusuf Salim: Homocysteine and Cardiovascular Disease: A Critical Review of the Epidemiologic Evidence. Ann Intern Med. 1999; 131:363-375.

^3 The Homocysteine Studies Collaboration: Homocysteine and Risk of lschemic Heart Disease and Stroke. JAMA 2002; Vol 288, No. 16:2015-2022.

^4 Refsum Helga, Smith A. David, Ueland Per M, Nexo Ebba, Clarke Robert, McPartlin Joseph, Johnston Carole, Engbaek Frode, Schneede Jorn, McPartlin Catherine, and Scott John M.: Facts and Recommendations about Total Homocysteine Determinations: An Expert Opinion. Clinical Chemistry 2004; 50(1):3-32.

^5 Kuzminski AM, Del Giacco EJ, Allen RH, et al: Effective Treatment of Cobalamin Deficiency with Oral Cobalamin. Blood 1998; 92:1191-1198.

^6 Troen AM, Mitchell B, Sorensen B, Wener MH, Johnston A, Wood B, Selhub J, McTiernan A, Yasui Y, Oral E, Potter JD, and Ulrich CM: Unmetabolized Folic Acid in Plasma is Associated with Reduced Natural Killer Cell Cytotoxicity among Postmenopausal Women. Journal of Nutrition 2006 Jan; 136(1): 189-194.

Rev. 10/19

PRINCIPAL DISPLAY PANEL - 90 Tablet Bottle Label

NIVAGEN

75834-080-90

Niva-Fol™
Tablets

Medical Food

90 Tablets

Do not use this product if the inner
safety seal under the cap is torn,
broken, or missing.